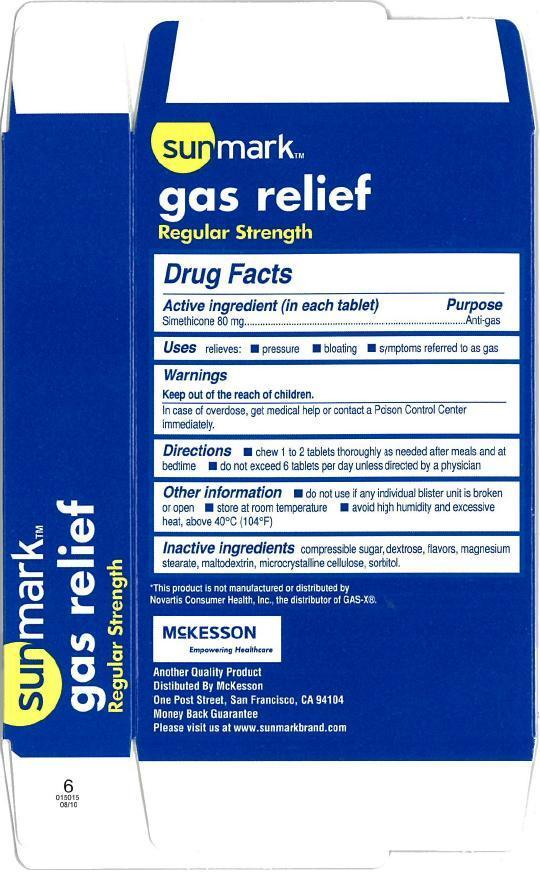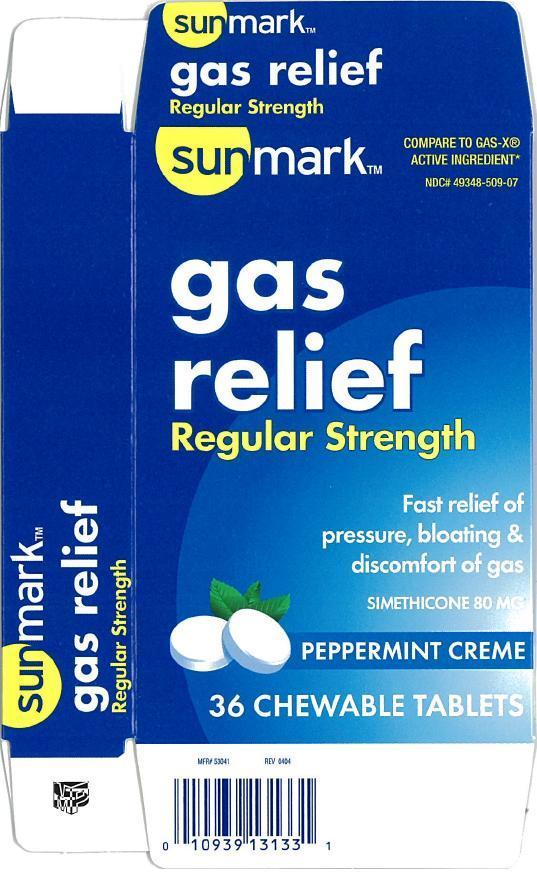 DRUG LABEL: Sunmark Gas relief
NDC: 49348-509 | Form: TABLET, CHEWABLE
Manufacturer: McKesson
Category: otc | Type: HUMAN OTC DRUG LABEL
Date: 20140410

ACTIVE INGREDIENTS: DIMETHICONE 80 mg/1 1
INACTIVE INGREDIENTS: RAW SUGAR; DEXTROSE; MAGNESIUM STEARATE; MALTODEXTRIN; CELLULOSE, MICROCRYSTALLINE; SORBITOL

Sunmark Gas Relief

Active ingredient (in each tablet)

Simethicone 80 mg

Purpose

Anti-gas

Uses

relieves

- pressure
- bloating
- symptoms referred to as gas

Warnings

Keep out of reach of children. In case of overdose, get medical help or contact a Poison Control Center immediately.

Directions

- chew 1 to 2 tablets thoroughly as needed after meals and at bedtime
- do not exceed 6 tablets per day unless directed by a physician.

Other information

- do not use if any individual blister unit is broken or open.
- store at room temperature.
- avoid high humidity and excessive heat, above 40°C (104°F)

Inactive ingredients

compressible sugar, dextrose, flavors, magnesium stearate, maltodextrin, microcrystalline cellulose, sorbitol

Principal Display Panel

Sunmark

COMPARE TO GAS-X® ACTIVE INGREDIENT

gas relief

Regular Strength

Fast relief of pressure, bloating & discomfort of gas

SIMETHICONE 80 mg

Peppermint creme

36 Chewable Tablets